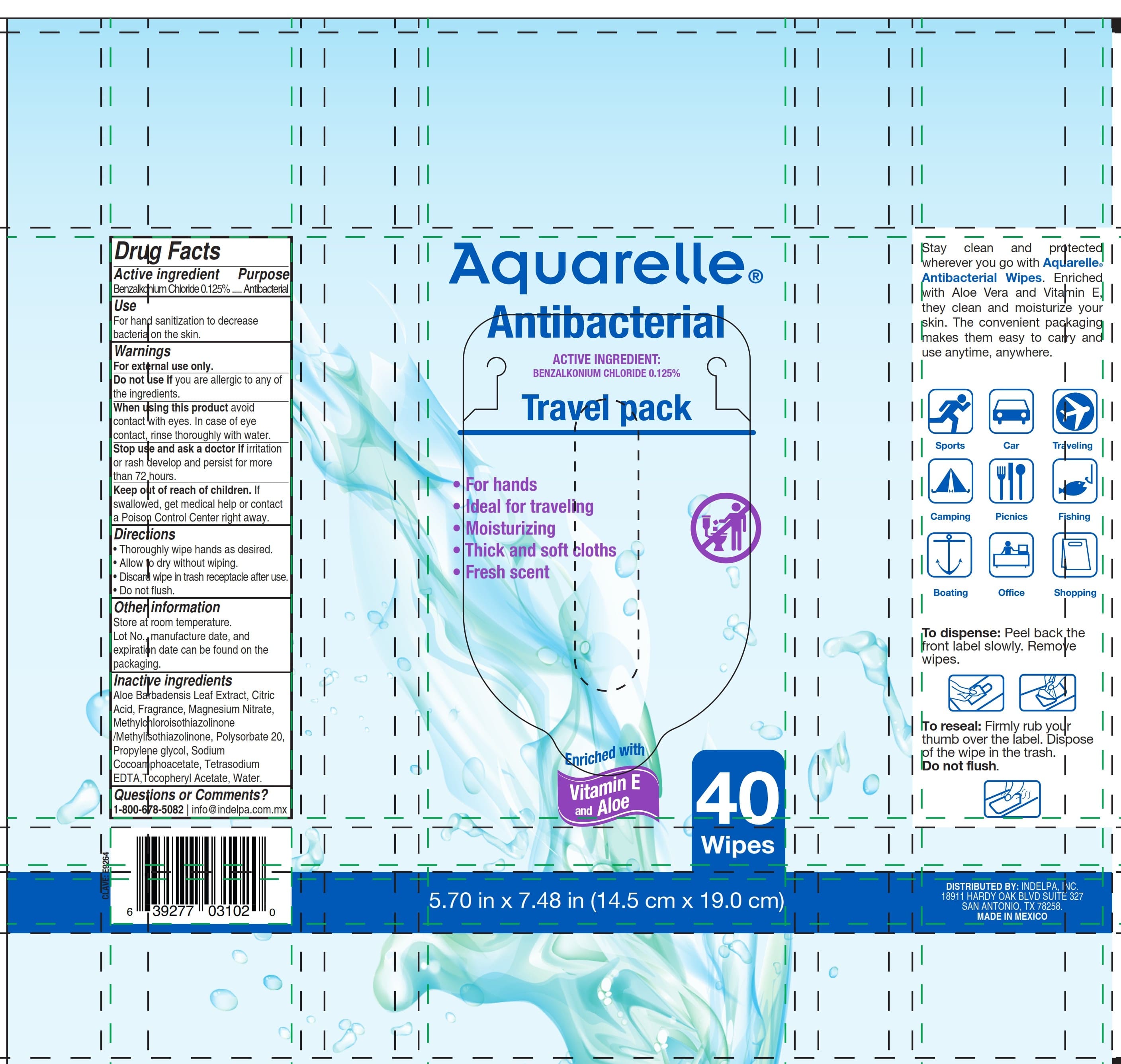 DRUG LABEL: Aquarrelle Antibacterial Wipes 40
NDC: 85718-001 | Form: CLOTH
Manufacturer: Kimberly-Clark De Mexico, S.A.B. de C.V.
Category: otc | Type: HUMAN OTC DRUG LABEL
Date: 20260205

ACTIVE INGREDIENTS: BENZALKONIUM CHLORIDE 0.125 mg/1 1
INACTIVE INGREDIENTS: ALOE BARBADENSIS LEAF; POLYSORBATE 20; WATER; SODIUM COCOAMPHOACETATE; CITRIC ACID; METHYLCHLOROISOTHIAZOLINONE/METHYLISOTHIAZOLINONE MIXTURE; MAGNESIUM NITRATE; PROPYLENE GLYCOL; .ALPHA.-TOCOPHEROL ACETATE; TETRASODIUM EDTA

Aquarelle Antibacterial 40

Purpose

Active ingredient .....................Purpose
Benzalkonium chloride 0.125% Antibacterial

Use

For hand sanitization to decrease bacteria on the skin.

Warnings

For external use only.

Do not use if

you are allergic to any of the ingredients

When using this product

avoid contact with eyes. In case of eye contact, rinse thoroughly with water.

Stop use and ask doctor if

irritation or rash develop and persist for more than 72 hours.

Keep out of reach of children

If swallowed, get medical help or contact a Poison Control Center right away

Warnings

For external use only

Directions

- Thoroughly wipe hands as desired.
- Allow to dry without wiping.
- Discard wipe in trash receptacle after use.
- Do not flush.

Other information

Store at room temperature.

Lot. No., manufacture date and expiration date can be found on the packaging.

Directions

• Thoroughly wipe hands as desired.
• Allow to dry without wiping.
• Discard wipe in trash receptacle after use.
• Do not flush

Inactive ingredients

Aloe Barbadensis Leaf Extract, Citric Acid, Fragrance, Magnesium Nitrate, Methylchloroisothiazolinone /Methylisothiazolinone, Polysorbate 20, Propylene glycol, Sodium Cocoamphoacetate, Tetrasodium EDTA,Tocopheryl Acetate, Water.

Questions or Comments?

1-800-678-5082 info@indelpa.com.mx

PACKAGE LABEL

Aquarelle®

Antibacterial

ACTIVE INGREDIENT:

BENZALKONIUM CHLORIDE 0.125%

Travel pack

- For hands
- Ideal for traveling
- Moisturizing
- Thick and soft cloths
- Fresh scent

Enriched with Vitamin E and Aloe

40 wipes

5.70 inx 7.48 in (14.5cmx19cm)

Distributed by: INDELPA INC

18911 Hardy Oak Blvd Suite 327

San Antonio, TX 78258

MADE IN MEXICO